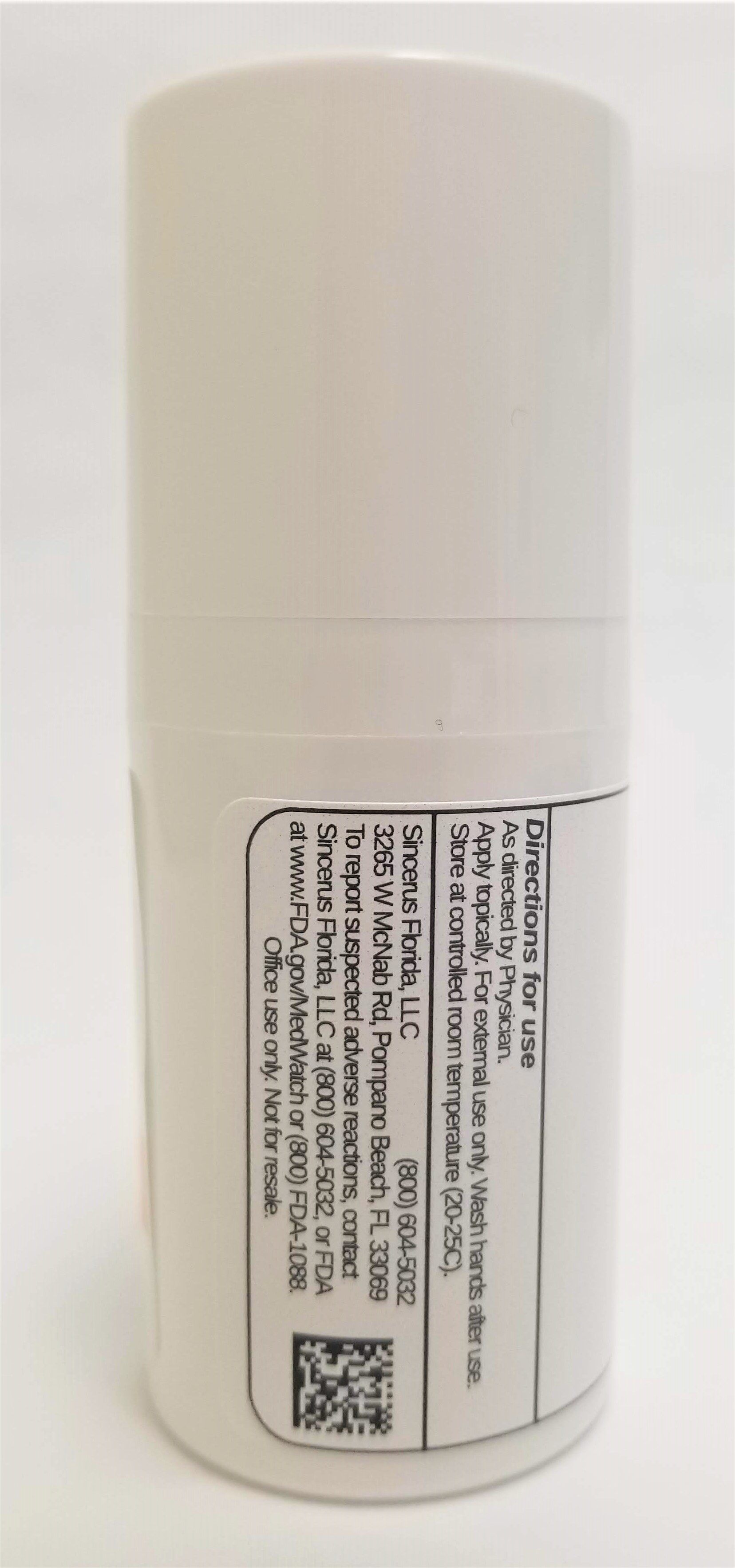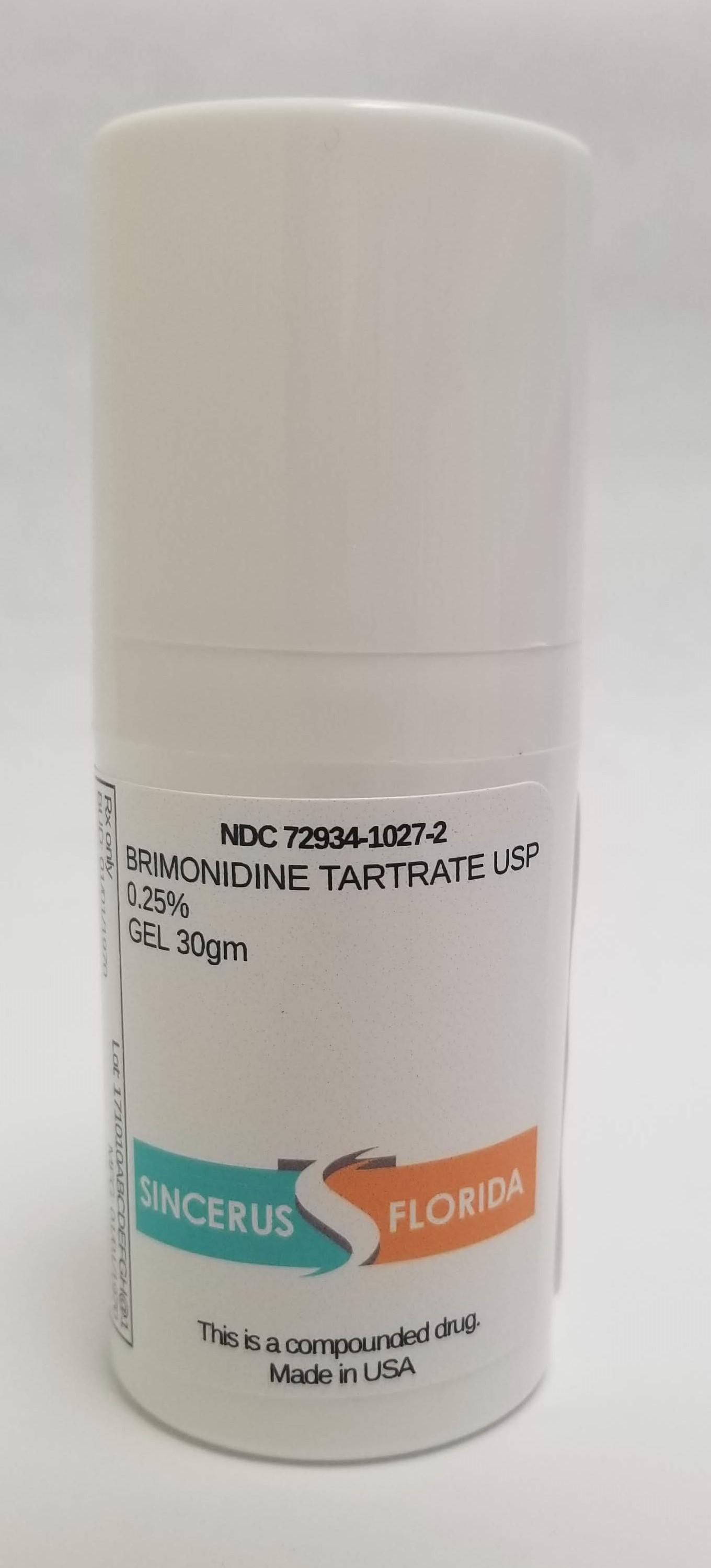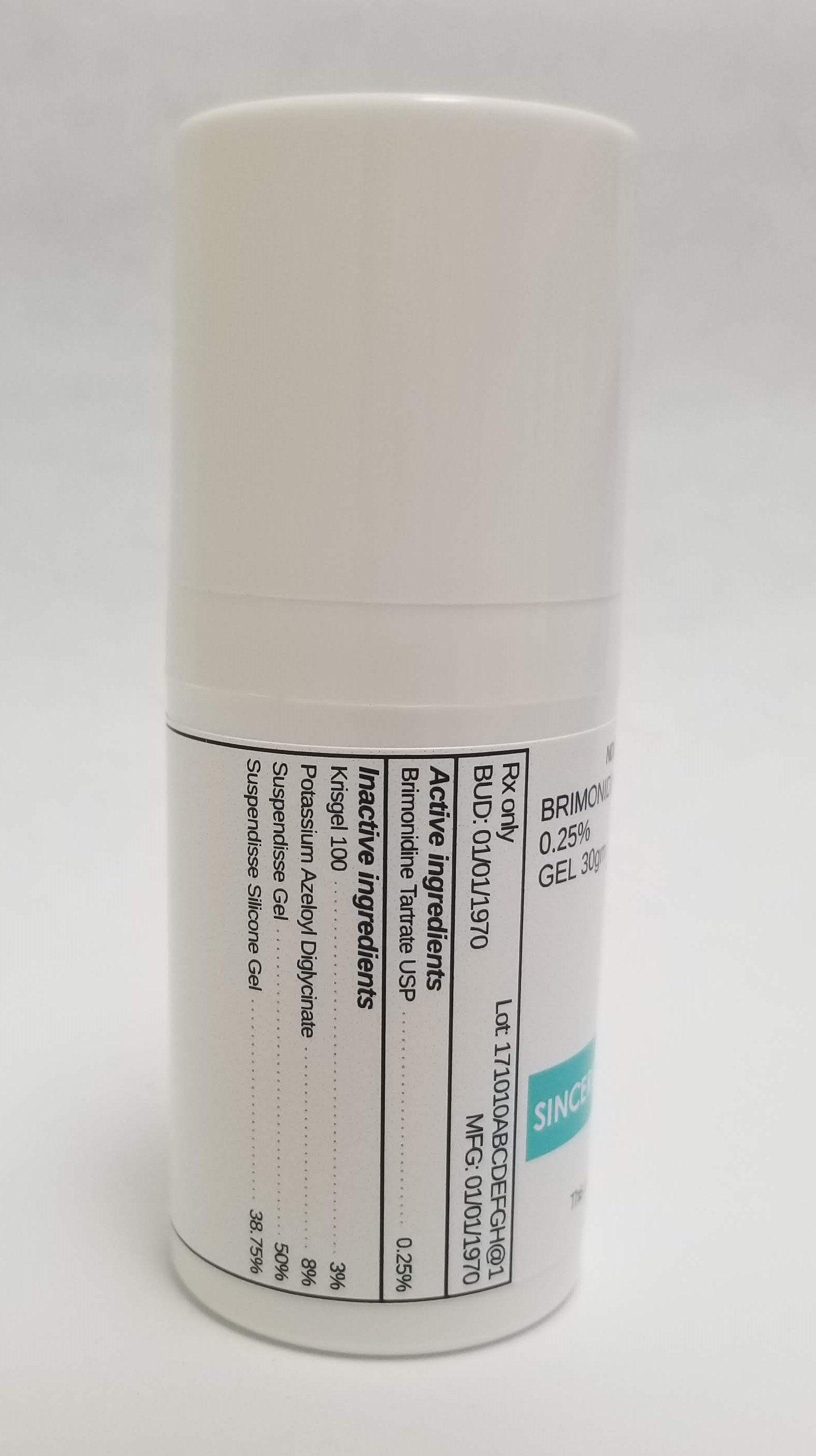 DRUG LABEL: BRIMONIDINE TARTRATE 0.25% / POTASSIUM AZELOYL DIGLYCINATE 8%
NDC: 72934-1027 | Form: GEL
Manufacturer: Sincerus Florida, LLC
Category: prescription | Type: HUMAN PRESCRIPTION DRUG LABEL
Date: 20190515

ACTIVE INGREDIENTS: BRIMONIDINE TARTRATE 0.25 g/100 g

BRIMONIDINE TARTRATE 0.25% / POTASSIUM AZELOYL DIGLYCINATE 8%